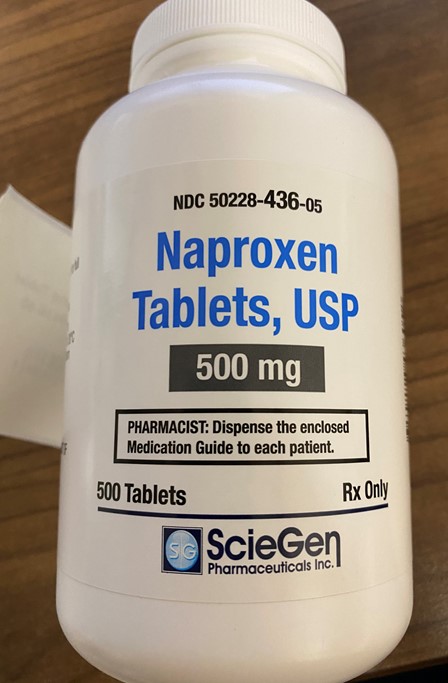 DRUG LABEL: Naproxen
NDC: 80175-0436 | Form: TABLET
Manufacturer: Central Packaging
Category: prescription | Type: HUMAN PRESCRIPTION DRUG LABEL
Date: 20210225

ACTIVE INGREDIENTS: NAPROXEN 500 mg/1 1

INDICATIONS AND USAGE

Naproxen Tablets are indicated for:
the relief of the signs and symptoms of:

rheumatoid arthritis
osteoarthritis
ankylosing spondylitis
polyarticular juvenile idiopathic arthritis
tendonitis
bursitis
acute gout

the management of:

pain
primary dysmenorrhea